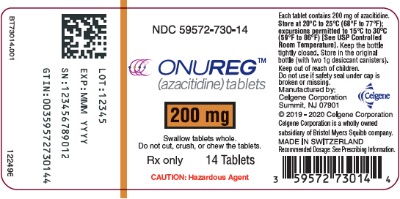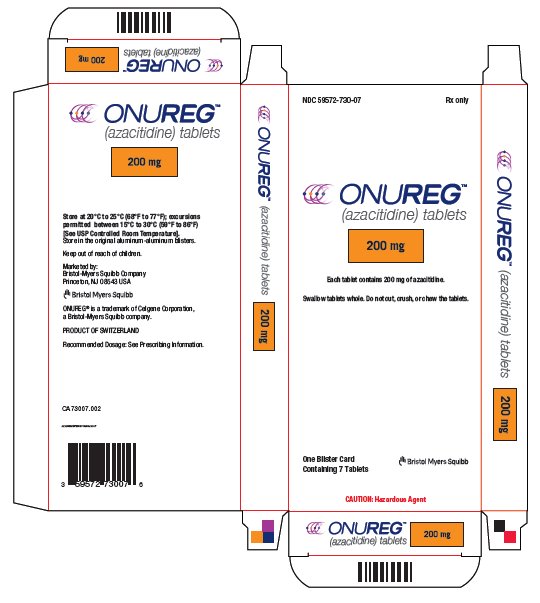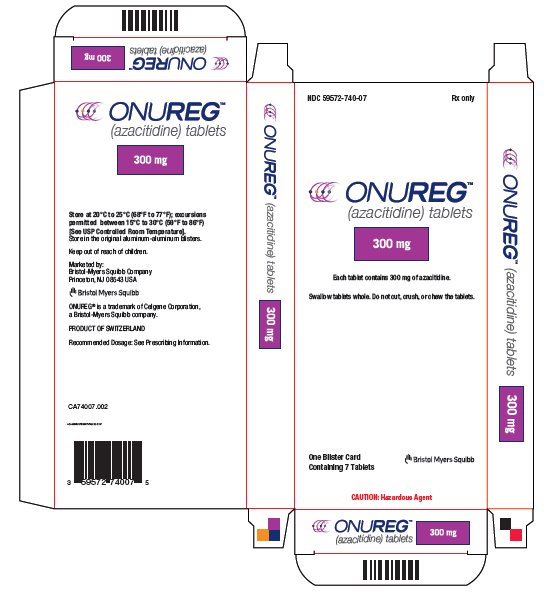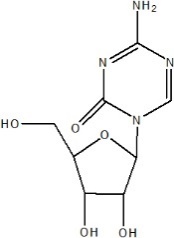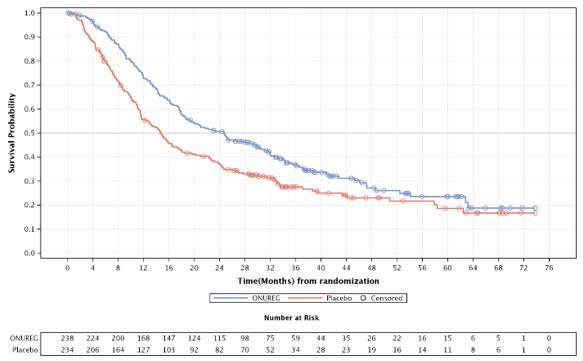 DRUG LABEL: ONUREG
NDC: 59572-730 | Form: TABLET, FILM COATED
Manufacturer: Celgene Corporation
Category: prescription | Type: HUMAN PRESCRIPTION DRUG LABEL
Date: 20221026

ACTIVE INGREDIENTS: AZACITIDINE 200 mg/1 1
INACTIVE INGREDIENTS: MANNITOL; MICROCRYSTALLINE CELLULOSE; CROSCARMELLOSE SODIUM; MAGNESIUM STEARATE

HIGHLIGHTS OF PRESCRIBING INFORMATION

These highlights do not include all the information needed to use ONUREG safely and effectively. See full prescribing information for ONUREG.
ONUREG (azacitidine) tablets, for oral use
Initial U.S. Approval: 2004

1 INDICATIONS AND USAGE

ONUREG is a nucleoside metabolic inhibitor indicated for continued treatment of adult patients with acute myeloid leukemia who achieved first complete remission (CR) or complete remission with incomplete blood count recovery (CRi) following intensive induction chemotherapy and are not able to complete intensive curative therapy (1).

2 DOSAGE AND ADMINISTRATION

- Do not substitute ONUREG for intravenous or subcutaneous azacitidine. The indications and dosing regimen for ONUREG differ from that of intravenous or subcutaneous azacitidine (2.1, 5.1).
- Administer ONUREG 300 mg orally once daily on Days 1 through 14 of each 28-day cycle (2.2).
- Administer an antiemetic before each dose for at least the first 2 cycles (2.2).

3 DOSAGE FORMS AND STRENGTHS

Tablets: 200 mg and 300 mg (3).

4 CONTRAINDICATIONS

History of severe hypersensitivity to azacitidine or its components (4).

5 WARNINGS AND PRECAUTIONS

- Risks of Substitution with Other Azacitidine Products: Do not substitute ONUREG for intravenous or subcutaneous azacitidine (2.1, 5.1).
- Myelosuppression: Monitor complete blood counts every other week for the first 2 cycles and prior to the start of each cycle thereafter. Increase monitoring to every other week for the 2 cycles after any dose reduction. Withhold and then resume at same or reduced dose or discontinue ONUREG based on severity (2.3, 5.2).
- Embryo-Fetal Toxicity: Can cause fetal harm. Advise patients of the potential risk to a fetus and use of effective contraception (5.4, 8.1, 8.3).

6 ADVERSE REACTIONS

The most common adverse reactions (≥ 10%) are nausea, vomiting, diarrhea, fatigue/asthenia, constipation, pneumonia, abdominal pain, arthralgia, decreased appetite, febrile neutropenia, dizziness, and pain in extremity (6).

To report SUSPECTED ADVERSE REACTIONS, contact Bristol-Myers Squibb Company at 1-800-721-5072 or FDA at 1-800-FDA-1088 or www.fda.gov/medwatch.

8 USE IN SPECIFIC POPULATIONS

Lactation: Advise not to breastfeed (8.2).

FULL PRESCRIBING INFORMATION

1 INDICATIONS AND USAGE

ONUREG is indicated for continued treatment of adult patients with acute myeloid leukemia who achieved first complete remission (CR) or complete remission with incomplete blood count recovery (CRi) following intensive induction chemotherapy and are not able to complete intensive curative therapy.

2 DOSAGE AND ADMINISTRATION

2.1 Important Administration Information

Do not substitute ONUREG for intravenous or subcutaneous azacitidine. The indications and dosing regimen for ONUREG differ from that of intravenous or subcutaneous azacitidine [see Warnings and Precautions (5.1)].

2.2 Recommended Dosage

The recommended dosage of ONUREG is 300 mg orally once daily with or without food on Days 1 through 14 of each 28-day cycle. Continue ONUREG until disease progression or unacceptable toxicity.

Administer an antiemetic 30 minutes prior to each dose of ONUREG for the first 2 cycles. Antiemetic prophylaxis may be omitted after 2 cycles if there has been no nausea and vomiting.

If the absolute neutrophil count (ANC) is less than 0.5 Gi/L on Day 1 of a cycle, do not administer ONUREG. Delay the start of the cycle until the ANC is 0.5 Gi/L or more.

Instruct patients on the following:

- Swallow tablets whole. Do not cut, crush, or chew the tablets.
- Take a dose about the same time each day.
- If a dose of ONUREG is missed, or not taken at the usual time, take the dose as soon as possible on the same day, and resume the normal schedule the following day. Do not take 2 doses on the same day.
- If a dose is vomited, do not take another dose on the same day. Resume the normal schedule the following day.

ONUREG is a hazardous drug. Follow applicable special handling and disposal procedures.^1

2.3 Monitoring and Dosage Modifications for Adverse Reactions

Monitor complete blood count every other week for the first 2 cycles and prior to the start of each cycle thereafter. Increase monitoring to every other week for the 2 cycles after any dose reduction for myelosuppression.

The recommended dosage modifications for adverse reactions are provided in Table 1.

Table 1: Recommended Dosage Modifications for Adverse Reactions
Adverse Reaction | Severity | Recommended Dosage Modification
Myelosuppression [see Warnings and Precautions (5.2)] | Neutrophils less than 0.5 Gi/L on Cycle Day 1 | - Interrupt treatment. Resume at the same dose once neutrophils return to 0.5 Gi/L or higher.
Myelosuppression [see Warnings and Precautions (5.2)] | Neutrophils less than 1 Gi/L with fever at anytime | First Occurrence; - Interrupt treatment. Resume at the same dose once neutrophils return to 1 Gi/L or higher.; Occurrence in 2 Consecutive Cycles; - Interrupt treatment. After neutrophils return to 1 Gi/L or higher, resume at reduced dose of 200 mg. - If a patient continues to experience febrile neutropenia after dose reduction, reduce the treatment duration by 7 days. - If febrile neutropenia reoccurs after dose and schedule reduction, discontinue ONUREG.
Myelosuppression [see Warnings and Precautions (5.2)] | Platelets less than 50 Gi/L with bleeding | First Occurrence; - Interrupt dose. Resume at the same dose once platelets return to 50 Gi/L or higher.; Occurrence in 2 Consecutive Cycles; - Interrupt dose. After platelets return to 50 Gi/L or higher, resume at reduced dose of 200 mg. - If a patient continues to experience thrombocytopenia with bleeding after dose reduction, reduce the treatment duration by 7 days. - If thrombocytopenia with bleeding reoccurs after dose and schedule reduction, discontinue ONUREG.
Gastrointestinal Toxicity [see Adverse Reactions (6.1)] | Grade 3 or 4 Nausea or Vomiting | - Interrupt dose. Resume at the same dose once toxicity has resolved to Grade 1 or lower. - If toxicity reoccurs, interrupt dose until resolved to Grade 1 or lower. Resume at reduced dose of 200 mg. - If a patient continues to experience the toxicity after dose reduction, reduce the treatment duration by 7 days. - If the toxicity continues or reoccurs after dose and schedule reduction, discontinue ONUREG.
Gastrointestinal Toxicity [see Adverse Reactions (6.1)] | Grade 3 or 4 Diarrhea | - Interrupt dose. Resume at the same dose once toxicity has resolved to Grade 1 or lower. - If toxicity reoccurs, interrupt dose until resolved to Grade 1 or lower. Resume at reduced dose of 200 mg. - If a patient continues to experience the toxicity after dose reduction, reduce the treatment duration by 7 days. - If the toxicity continues or reoccurs after dose and schedule reduction, discontinue ONUREG.
Other Adverse Reactions [see Adverse Reactions (6.1)] | Grade 3 or 4 | - Interrupt dose and provide medical support. Resume at the same dose once toxicity has resolved to Grade 1 or lower. - If toxicity re-occurs, interrupt dose until resolved to Grade 1 or lower. Resume at reduced dose of 200 mg. - If a patient continues to experience the toxicity after dose reduction, reduce the treatment duration by 7 days. - If the toxicity continues or reoccurs after dose and schedule reduction, discontinue ONUREG.

3 DOSAGE FORMS AND STRENGTHS

Tablets:

- 200 mg, pink, oval, film-coated tablet with debossed "200" on one side and "ONU" on the other side.
- 300 mg, brown, oval, film-coated tablet with debossed "300" on one side and "ONU" on the other side.

4 CONTRAINDICATIONS

ONUREG is contraindicated in patients with known severe hypersensitivity to azacitidine or its components [see Adverse Reactions (6.2), Description (11)].

5 WARNINGS AND PRECAUTIONS

5.1 Risks of Substitution with Other Azacitidine Products

Due to substantial differences in the pharmacokinetic parameters [see Clinical Pharmacology (12.3)], the recommended dose and schedule for ONUREG are different from those for the intravenous or subcutaneous azacitidine products. Treatment of patients using intravenous or subcutaneous azacitidine at the recommended dosage of ONUREG may result in a fatal adverse reaction. Treatment of patients using ONUREG at the doses recommended for intravenous or subcutaneous azacitidine may not be effective.

Do not substitute ONUREG for intravenous or subcutaneous azacitidine [see Dosage and Administration (2.1)].

5.2 Myelosuppression

New or worsening Grade 3 or 4 neutropenia and thrombocytopenia occurred in 49% and 22% of patients who received ONUREG, respectively. Febrile neutropenia occurred in 12%. A dose reduction was required for 7% and 2% of patients due to neutropenia and thrombocytopenia, respectively. Less than 1% of patients discontinued ONUREG due to either neutropenia or thrombocytopenia.

Monitor complete blood counts and modify the dosage as recommended [see Dosage and Administration (2.2, 2.3)]. Provide standard supportive care, including hematopoietic growth factors, if myelosuppression occurs.

5.3 Increased Early Mortality in Patients with Myelodysplastic Syndromes

In AZA-MDS-003 (NCT01566695), 216 patients with red blood cell transfusion-dependent anemia and thrombocytopenia due to myelodysplastic syndromes were randomized to ONUREG or placebo. One-hundred and seven patients received a median of 5 cycles of ONUREG 300 mg daily for 21 days of a 28-day cycle. Enrollment was discontinued early due to a higher incidence of early fatal and/or serious adverse reactions in patients who received ONUREG compared with placebo. The most frequent fatal adverse reaction was sepsis. The safety and effectiveness of ONUREG for treatment of myelodysplastic syndromes have not been established. Treatment of patients with myelodysplastic syndromes with ONUREG is not recommended outside of controlled trials.

5.4 Embryo-Fetal Toxicity

Based on the mechanism of action and findings in animals, ONUREG can cause fetal harm when administered to a pregnant woman. Azacitidine administered to pregnant rats via a single intraperitoneal dose less than the recommended human daily dose of oral azacitidine on a mg/m^2 basis caused fetal death and anomalies.

Advise pregnant women of the potential risk to a fetus. Advise females of reproductive potential to use effective contraception during treatment with ONUREG and for at least 6 months after the last dose. Advise males with female partners of reproductive potential to use effective contraception during treatment with ONUREG and for at least 3 months after the last dose [see Use in Specific Populations (8.1, 8.3)].

6 ADVERSE REACTIONS

The following clinically significant adverse reactions are described elsewhere in the labeling:

- Myelosuppression [see Warnings and Precautions (5.2)]

6.1 Clinical Trials Experience

Because clinical trials are conducted under widely varying conditions, adverse reaction rates observed in the clinical trials of a drug cannot be directly compared to rates in the clinical trials of another drug and may not reflect the rates observed in practice.

Acute Myeloid Leukemia

The safety of ONUREG was evaluated in QUAZAR [see Clinical Studies (14)]. Patients received ONUREG 300 mg (N=236) or placebo (N=233) orally once daily on Days 1 through 14 of each 28-day cycle. Among patients who received ONUREG, 71% were exposed for 6 months or longer, and 49% were exposed for greater than one year. The median duration of exposure to ONUREG was 11.6 months (range: 0.5 to 74.3 months) and the median number of cycles was 12 (range: 1 to 82 cycles).

Serious adverse reactions occurred in 15% of patients who received ONUREG. Serious adverse reactions in ≥ 2% of patients who received ONUREG were pneumonia (8%) and febrile neutropenia (7%). One fatal adverse reaction (sepsis) occurred in a patient who received ONUREG.

Permanent discontinuation of ONUREG due to an adverse reaction occurred in 8% of patients. Adverse reactions which resulted in permanent discontinuation of ONUREG in > 1% of patients included nausea (2.1%), diarrhea (1.7%), and vomiting (1.3%). Interruptions of ONUREG due to an adverse reaction occurred in 35% of patients. Adverse reactions which required an interruption of ONUREG in > 5% of patients included neutropenia (20%), thrombocytopenia (8%), and nausea (6%).

Dose reductions of ONUREG due to an adverse reaction occurred in 14% of patients. Adverse reactions which required a dose reduction in > 1% of patients included neutropenia (6%), diarrhea (3.4%), thrombocytopenia (1.7%), and nausea (1.7%).

The most common (≥ 10%) adverse reactions were nausea, vomiting, diarrhea, fatigue/asthenia, constipation, pneumonia, abdominal pain, arthralgia, decreased appetite, febrile neutropenia, dizziness, and pain in extremity.

Table 2 summarizes the adverse reactions in QUAZAR.

Table 2: Adverse Reactions (≥ 5%) in Patients with AML Who Received ONUREG with a Difference Between Arms of > 2% Compared to Placebo in QUAZAR
Adverse Reaction | ONUREG (N=236) |  | Placebo (N=233)
Adverse Reaction | All Grades (%) | Grade 3 or 4 (%) | All Grades (%) | Grade 3 or 4 (%)
Gastrointestinal disorders
Nausea | 65 | 3 | 24 | < 1
Vomiting | 60 | 3 | 10 | 0
Diarrhea | 50 | 5 | 21 | 1
Constipation | 39 | 1 | 24 | 0
Abdominal paina | 22 | 2 | 13 | < 1
General disorders and administration site conditions
Fatigue / astheniab | 44 | 4 | 25 | 1
Infections
Pneumoniac | 27 | 9 | 17 | 5
Musculoskeletal and connective tissue disorders
Arthralgia | 14 | 1 | 10 | < 1
Pain in extremity | 11 | < 1 | 5 | 0
Metabolism and nutrition disorders
Decreased appetite | 13 | 1 | 6 | 1
Blood and lymphatic disorders
Febrile neutropenia | 12 | 11 | 8 | 8
Nervous system disorders
Dizziness | 11 | 0 | 9 | 0
a Grouped term includes abdominal pain, abdominal pain upper, abdominal discomfort, and gastrointestinal pain.
b Grouped term includes fatigue and asthenia.
c Broad scope term includes influenza, pneumonia, respiratory tract infection, respiratory tract infection viral, bronchopulmonary aspergillosis, lung infection, Staphylococcal infection, atypical pneumonia, lower respiratory tract infection, lung abscess, Pneumocystis jirovecii pneumonia, pneumonia bacterial, pneumonia fungal, Pseudomonas infection, hemoptysis, productive cough, pleural effusion, atelectasis, pleuritic pain, rales, Enterobacter test positive, and Hemophilus test positive.

Clinically relevant adverse reactions that did not meet criteria for inclusion in Table 2 were weight decreased (4%) in patients who received ONUREG.

Neutropenia, thrombocytopenia, and anemia of any grade occurred in 74%, 65%, and 25% of patients who received ONUREG. Table 3 summarizes select Grades 3 or 4 hematological laboratory abnormalities in QUAZAR.

Table 3: Selected Hematological Laboratory Abnormalities That Worsened from Baseline in Patients Who Received ONUREG in QUAZAR
 | ONUREG |  | Placebo
Laboratory Abnormality | Baseline Grade 0-2 N | Post-Baseline Grade 3 or 4 n (%) | Baseline Grade 0-2 N | Post-Baseline Grade 3 or 4 n (%)
Neutropenia | 223 | 109 (49) | 217 | 50 (23)
Thrombocytopenia | 222 | 46 (21) | 212 | 22 (10)
Anemia | 229 | 10 (4) | 223 | 7 (3)

6.2 Postmarketing Experience

The following adverse reactions have been identified during postapproval use of intravenous or subcutaneous azacitidine. Because these reactions are reported voluntarily from a population of uncertain size, it is not always possible to reliably estimate their frequency or establish a causal relationship to drug exposure.

- Hypersensitivity reaction
- Interstitial lung disease
- Tumor lysis syndrome
- Sweet's syndrome (acute febrile neutrophilic dermatosis)
- Necrotizing fasciitis (including fatal cases)
- Differentiation syndrome

8 USE IN SPECIFIC POPULATIONS

8.1 Pregnancy

Risk Summary

Based on its mechanism of action [see Clinical Pharmacology (12.1)] and findings in animals, ONUREG can cause fetal harm when administered to a pregnant woman. There are no available data on ONUREG use in pregnant women to evaluate for a drug-associated risk. Azacitidine was teratogenic and caused embryo-fetal lethality in animals at doses less than the recommended human daily dose of oral azacitidine on a mg/m^2 basis (see Data). Advise pregnant women of the potential risk to the fetus.

The estimated background of major birth defects and miscarriage for the indicated population is unknown. All pregnancies have a background risk of birth defect, loss, or other adverse outcomes. In the U.S. general population, the estimated background risk of major birth defects and miscarriage in clinically recognized pregnancies is 2% to 4% and 15% to 20%, respectively.

Data

Animal Data

No reproductive or developmental toxicity studies have been conducted with oral azacitidine.

Early embryotoxicity studies in mice revealed a 44% frequency of intrauterine embryonal death (increased resorption) after a single intraperitoneal injection of 6 mg/m^2 azacitidine (at doses less than the recommended human daily dose of oral azacitidine on a mg/m^2 basis) on gestation Day 10. Developmental abnormalities in the brain have been detected in mice given azacitidine on or before gestation Day 15 at doses of approximately 3 to 12 mg/m^2 (at doses less than the recommended human daily dose on a mg/m^2 basis).

In rats, azacitidine was clearly embryotoxic when given an intraperitoneal injection on gestation Days 4 to 8 (postimplantation) at a dose of 6 mg/m^2 (at doses less than the recommended human daily dose on a mg/m^2 basis), although treatment in the preimplantation period (on gestation Days 1 to 3) had no adverse effect on the embryos. Azacitidine caused multiple fetal abnormalities in rats after a single intraperitoneal dose of 3 to 12 mg/m^2 (at doses less than the recommended human daily dose on a mg/m^2 basis) given on gestation Days 9, 10, 11, or 12. In this study, azacitidine caused fetal death when administered at 3 to 12 mg/m^2 on gestation Days 9 and 10; average live animals per litter was reduced to 9% of control at the highest dose on gestation Day 9. Fetal anomalies included: CNS anomalies (exencephaly/encephalocele), limb anomalies (micromelia, club foot, syndactyly, oligodactyly), and others (micrognathia, gastroschisis, edema, and rib abnormalities).

8.2 Lactation

Risk Summary

There are no data regarding the presence of azacitidine in human milk or the effects on the breastfed child or milk production. Because of the potential for serious adverse reactions in the breastfed child, advise women not to breastfeed during treatment with ONUREG and for 1 week after the last dose.

8.3 Females and Males of Reproductive Potential

ONUREG can cause embryo-fetal harm when administered to pregnant women [see Use in Specific Populations (8.1)].

Pregnancy Testing

Pregnancy testing is recommended for females of reproductive potential before starting ONUREG.

Contraception

Females

Advise females of reproductive potential to use effective contraception during treatment with ONUREG and for at least 6 months after the last dose.

Males

Advise males with female partners of reproductive potential to use effective contraception during treatment with ONUREG and for at least 3 months after the last dose.

Infertility

Based on animal data, ONUREG may impair male or female fertility [see Nonclinical Toxicology (13.1)].

8.4 Pediatric Use

The safety and effectiveness of ONUREG in pediatric patients have not been established.

8.5 Geriatric Use

Of the 238 patients in QUAZAR who received ONUREG, 72% were 65 years of age or older, while 12% were 75 years of age or older. No overall differences in safety or effectiveness of ONUREG were observed between these patients and younger patients.

8.6 Renal Impairment

Monitor patients with severe renal impairment (creatinine clearance [CLcr] 15 to 29 mL/min calculated by Cockcroft-Gault formula) more frequently for adverse reactions and modify the ONUREG dosage for adverse reactions [see Dosage and Administration (2.3)].

No dose adjustment of ONUREG is recommended for patients with mild to severe renal impairment (CLcr 15 to 89 mL/min) [see Clinical Pharmacology (12.3)].

8.7 Hepatic Impairment

ONUREG has not been studied in patients with pre-existing severe hepatic impairment (total bilirubin > 3 × ULN).

A recommended dosage of ONUREG has not been established for patients with moderate hepatic impairment (total bilirubin > 1.5 to 3 × ULN).

No dose adjustment of ONUREG is recommended for patients with mild hepatic impairment (total bilirubin ≤ ULN and AST > ULN, or total bilirubin 1 to 1.5 × ULN and any AST) [see Clinical Pharmacology (12.3)].

11 DESCRIPTION

Azacitidine is a nucleoside metabolic inhibitor with a molecular formula of C8H12N4O5 and a molecular weight of 244 g/mol. The chemical name is: 4-amino-1-β-D-ribofuranosyl-s-triazin-2(1H)-one and the chemical structural is:

Azacitidine is a white to off-white solid. Azacitidine was found to be soluble in aqueous media across a pH range from 1.0 to 7.0.

ONUREG (azacitidine) is supplied as film-coated tablets containing 200 mg or 300 mg of azacitidine for oral use. Each core tablet contains the following inactive ingredients: croscarmellose sodium, magnesium stearate, mannitol, and silicified microcrystalline cellulose. The 200 and 300 mg tablet coating contains hypromellose, lactose monohydrate, polyethylene glycol, titanium dioxide, and triacetin. In addition, the 200 mg tablet coating contains iron oxide red and the 300 mg tablet coating contains black iron oxide, iron oxide red, and iron oxide yellow.

12 CLINICAL PHARMACOLOGY

12.1 Mechanism of Action

Azacitidine is a pyrimidine nucleoside analog of cytidine that inhibits DNA/RNA methyltransferases. Azacitidine is incorporated into DNA and RNA following cellular uptake and enzymatic biotransformation to nucleotide triphosphates.

Incorporation of azacitidine into the DNA of cancer cells in vitro, including acute myeloid leukemia cells, inhibited DNA methyltransferases, reduced DNA methylation and altered gene expression, including re-expression of genes regulating tumor suppression and cell differentiation. Incorporation of azacitidine into the RNA of cancer cells, including leukemic cells, inhibited RNA methyltransferases, reduced RNA methylation, decreased RNA stability and decreased protein synthesis.

Antileukemic activity of azacitidine was demonstrated by reduction of cell viability and induction of apoptosis in AML cell lines in vitro. Azacitidine decreased tumor burden and increased survival in leukemic tumor models in vivo.

12.2 Pharmacodynamics

Greater reduction in global DNA methylation was observed with higher azacitidine plasma exposure in patients with AML administered ONUREG for 14 days of a 28-day cycle.

12.3 Pharmacokinetics

The systemic exposure of azacitidine is approximately dose proportional over the dose range of 120 mg to 600 mg once daily of ONUREG (0.4 to 2 times the recommended dosage). Following a single 300 mg dose of ONUREG, the mean (coefficient of variation [CV%]) Cmax of azacitidine was 145 ng/mL (64%) and the mean AUC of azacitidine was 242 ng h/mL (65%). No accumulation was observed following ONUREG 300 mg once daily.

Absorption

The mean oral bioavailability is approximately 11% relative to subcutaneous administration. The median time to peak plasma concentration of azacitidine is 1 hour.

Effect of Food

A high-fat, high-calorie meal (approximately 800 to 1000 calories, 50% fat) did not affect AUC0-INF and decreased Cmax by 21%.

Distribution

The mean (CV%) apparent volume of distribution (Vz/F) of azacitidine is 881 L (67%). The in vitro serum protein binding of azacitidine is approximately 6% to 12%. The blood-to-plasma ratio is approximately 0.3.

Elimination

The mean (CV%) terminal half-life is approximately 0.5 hours (27%) and the apparent clearance (CL/F) is 1240 L/hour (64%).

Metabolism

Azacitidine undergoes spontaneous hydrolysis and deamination mediated by cytidine deaminase.

Excretion

Following the administration of ONUREG 300 mg orally once daily, < 2% of the dose was recovered unchanged in the urine.

Specific Populations

Age (46 years to 93 years), sex, body weight (39.3 kg to 129 kg), mild hepatic impairment (total bilirubin ≤ ULN and AST > ULN, or total bilirubin 1 to 1.5 × ULN and any AST), and mild to moderate renal impairment (CLcr 30 to 89 mL/min) have no clinically meaningful effect on the pharmacokinetics of oral azacitidine. The effects of race/ethnicity, moderate to severe hepatic impairment (total bilirubin > 1.5 × ULN and any AST), and severe renal impairment (CLcr 15 to 29 mL/min) on the pharmacokinetics of oral azacitidine is unknown.

Severe renal impairment increased azacitidine exposure by approximately 70% after a single or 41% after multiple subcutaneous daily administration.

Drug Interaction Studies

Effect of Gastric Acid Reducing Agents on Azacitidine:

Coadministration of omeprazole (a proton pump inhibitor) with ONUREG increased azacitidine AUC0-INF by 19% and had no effect on Cmax.

In Vitro Studies

Cytochrome P450 (CYP) Enzymes: Azacitidine does not inhibit CYP1A2, CYP2B6, CYP2C8, CYP2C9, CYP2C19, CYP2D6, CYP3A4, or CYP2E1 at clinically relevant concentrations. Azacitidine is not an inducer of CYP1A2, CYP2C19, or CYP3A.

Transporter Systems: Azacitidine is not a substrate of P-glycoprotein (P-gp). Azacitidine does not inhibit P-gp, breast cancer resistance protein (BCRP), organic anion transporters (OAT) OAT1 and OAT3, organic anion transporting polypeptides (OATP) OATP1B1 and OATP1B3, or organic cation transporter (OCT) OCT2 at clinically relevant concentrations.

13 NONCLINICAL TOXICOLOGY

13.1 Carcinogenesis, Mutagenesis, Impairment of Fertility

The potential carcinogenicity of azacitidine was evaluated in mice and rats. Azacitidine induced tumors of the hematopoietic system in female mice at 2.2 mg/kg (6.6 mg/m^2, approximately 4% of the recommended human daily dose of oral azacitidine on a mg/m^2 basis) administered intraperitoneal 3 times per week for 52 weeks. An increased incidence of tumors in the lymphoreticular system, lung, mammary gland, and skin was seen in mice treated with intraperitoneal azacitidine at 2 mg/kg (6 mg/m^2, approximately 3% of the recommended human daily dose of oral azacitidine on a mg/m^2 basis) once a week for 50 weeks. A tumorigenicity study in rats dosed twice weekly at 15 or 60 mg/m^2 (approximately 8% to 32% of the recommended human daily dose of oral azacitidine on a mg/m^2 basis) revealed an increased incidence of testicular tumors compared with controls.

The mutagenic and clastogenic potential of azacitidine was tested in in vitro bacterial systems Salmonella typhimurium strains TA100 and several strains of trpE8, Escherichia coli strains WP14 Pro, WP3103P, WP3104P, and CC103; in an in vitro forward gene mutation assay in mouse lymphoma cells and human lymphoblast cells; and in an in vitro micronucleus assay in mouse L5178Y lymphoma cells and Syrian hamster embryo cells. Azacitidine was mutagenic in bacterial and mammalian cell systems. The clastogenic effect of azacitidine was shown by the induction of micronuclei in L5178Y mouse cells and Syrian hamster embryo cells.

Administration of azacitidine by intraperitoneal injection to male mice at 9.9 mg/m^2 (at doses less than the recommended human daily dose on a mg/m^2 basis) daily for 3 days prior to mating with untreated female mice resulted in decreased fertility and loss of offspring during subsequent embryonic and postnatal development. Treatment of male rats 3 times per week for 11 or 16 weeks at doses of 15 to 30 mg/m^2 (at doses less than the recommended human daily dose on a mg/m^2 basis) resulted in decreased weight of the testes and epididymides, decreased sperm counts accompanied by decreased pregnancy rates, and increased loss of embryos in mated females. In a related study, male rats treated for 16 weeks at 24 mg/m^2 resulted in an increase in abnormal embryos in mated females when examined on Day 2 of gestation.

14 CLINICAL STUDIES

The efficacy of ONUREG was evaluated in QUAZAR (NCT01757535), a multicenter, randomized, double-blind, placebo-controlled study. Eligible patients were ages 55 years or older, had AML, and were within 4 months of achieving first complete remission (CR) or complete remission with incomplete blood count recovery (CRi) with intensive induction chemotherapy. Patients may have received consolidation (see Table 4). Patients were excluded if they were candidates for hematopoietic stem cell transplantation at the time of screening.

A total of 472 patients who completed induction with or without consolidation therapy were randomized 1:1 to receive ONUREG 300 mg (n=238) or placebo (n=234) orally on Days 1 through 14 of each 28-day cycle. Randomization was stratified by age at time of induction therapy (55 to 64 vs. ≥ 65 years), cytogenetic risk category at time of induction therapy (intermediate risk vs. poor risk), prior history of MDS/CMML (yes vs. no), and received consolidation therapy following induction therapy (yes vs. no). Baseline demographic and disease characteristics are shown in Table 4.

Table 4: Baseline Demographics and Disease-Related Characteristics in QUAZAR
Parameter | ONUREG (N=238) | Placebo (N=234)
Age (years)
Median (Min, Max) | 68.0 (55, 86) | 68.0 (55, 82)
Age Category, n (%)
< 65 years | 66 (28) | 68 (29)
65 years to < 75 years | 144 (61) | 142 (61)
≥ 75 years | 28 (12) | 24 (10)
Sex, n (%)
Male | 118 (50) | 127 (54)
Female | 120 (50) | 107 (46)
Race, n (%)
White | 216 (91) | 197 (84)
Black or African American | 2 (1) | 6 (3)
Asian | 6 (3) | 20 (9)
Other | 12 (5) | 11 (5)
Not Collected or Reported | 2 (1) | 0 (0)
ECOG Performance Status, n (%)
0 | 116 (49) | 111 (47)
1 | 101 (42) | 106 (45)
2 | 21 (9) | 15 (6)
3 | 0 (0) | 2 (1)
Cytogenetic Risk Status at Diagnosis, n (%)
Intermediate Risk^1 | 203 (85) | 203 (87)
Poor Risk^2 | 35 (15) | 31 (13)
Initial AML Classification, n (%)
AML with recurrent genetic abnormalities | 39 (16) | 46 (20)
AML with myelodysplasia-related changes | 49 (21) | 42 (18)
Therapy related myeloid neoplasms | 2 (1) | 0 (0)
AML not otherwise specified | 148 (62) | 145 (62)
Missing | 0 (0) | 1 (< 1)
Type of AML, n (%)
Primary (de novo) | 213 (89) | 216 (92)
Secondary | 25 (11) | 18 (8)
Induction Response
CR | 187 (79) | 197 (84)
CRi | 51 (21) | 37 (16)
Consolidation following induction therapy
None | 52 (22) | 42 (18)
1 cycle | 110 (46) | 102 (44)
2 cycles | 70 (29) | 77 (33)
3 cycles | 6 (3) | 13 (6)
Disease status at study baseline
CR | 185 (78) | 181 (77)
CRi | 44 (18) | 38 (16)
Not in CR or CRi | 9 (4) | 13 (6)
Not Reported | 0 | 2 (1)
AML=Acute Myeloid Leukemia, MDS=Myelodysplastic Syndrome, CMML=Chronic Myelomonocytic Leukemia, ECOG=Eastern Cooperative Oncology Group, CR=Morphologic Complete Remission, CRi=Morphologic complete remission with incomplete blood count recovery.
Source for Intermediate and Poor Risk: National Comprehensive Cancer Network Clinical Practice Guidelines in Oncology for Acute Myeloid Leukemia. National Comprehensive Cancer Network website. Available at http://www.nccn.org/professionals/physician_gls/PDF/aml.pdf. Accessed 01 Mar 2011.
^1 Intermediate risk was defined as normal cytogenetics +8, t(9;11), or Other undefined.
^2 Poor risk was defined as Complex (≥ 3 abnormalities): -5; 5q-; -7; 7q-; 11q23 - non t(9;11); inv(3); t(3;3); t(6;9); or t(9;22).

The efficacy of ONUREG was established on the basis of overall survival (OS). The trial demonstrated a statistically significant improvement in OS for patients randomized to ONUREG compared to placebo. A subgroup analysis showed consistency in the OS benefit for patients in either CR or CRi. The efficacy results are summarized in Table 5 and Figure 1.

Table 5: Efficacy Results (ITT Population) in QUAZAR
 | ONUREG (N=238) | Placebo (N=234)
Overall Survival
OS Events, n (%) | 158 (66) | 171 (73)
Median OS (95% CI) Months | 24.7 (18.7, 30.5) | 14.8 (11.7, 17.6)
Hazard Ratio (95% CI)^1 | 0.69 (0.55, 0.86)
p value^1 | 0.0009
^1 The hazard ratio is from a Cox proportional hazards model stratified by age (55 to 64 vs. ≥65 years), cytogenetic risk category at time of induction therapy (intermediate risk vs. poor risk), and received consolidation therapy (yes vs. no). The p-value is two-sided from a log-rank test stratified by the same factors.

Figure 1: Kaplan-Meier Curve for Overall Survival (ITT Population) in QUAZAR

15 REFERENCES

1. "OSHA Hazardous Drugs." OSHA. http://www.osha.gov/SLTC/hazardousdrugs/index.html

16 HOW SUPPLIED/STORAGE AND HANDLING

How Supplied

ONUREG tablets are available as:

- 200 mg: pink, oval, film-coated tablets with debossed "200" on one side and "ONU" on the other side.
- 300 mg: brown, oval, film-coated tablets with debossed "300" on one side and "ONU" on the other side.

Table 6 lists the package configurations and strengths.

Table 6: ONUREG Package Configurations and NDC Numbers
Package Configuration | Tablet Strength | NDC Number
One blister card containing 7 tablets | 200 mg | 59572-730-07
One blister card containing 7 tablets | 300 mg | 59572-740-07

Storage

- Store bottles at 20°C to 25°C (68°F to 77°F); excursions permitted between 15°C to 30°C (59°F to 86°F) [see USP Controlled Room Temperature].
  Keep bottle tightly closed.
  Store and dispense in the original bottle (with two desiccant canisters).
- Store blisters at 20°C to 25°C (68°F to 77°F); excursions permitted between 15°C to 30°C (59°F to 86°F) [see USP Controlled Room Temperature].
  Store in the original aluminum-aluminum blisters.

Handling and Disposal

ONUREG is a hazardous drug. Follow applicable special handling and disposal procedures.^1

If powder comes in contact with skin, immediately and thoroughly wash with soap and water. If powder comes in contact with mucous membranes, immediately flush the area with water.

17 PATIENT COUNSELING INFORMATION

Advise the patient to read the FDA-approved patient labeling (Patient Information).

Myelosuppression

Advise patients of the risk of myelosuppression with ONUREG and of the need to monitor complete blood counts before and during treatment [see Warnings and Precautions (5.2)].

Gastrointestinal Toxicity

Advise patients of the risk of gastrointestinal toxicity with ONUREG and of the potential need to use anti-emetic or anti-diarrheal medications during treatment [see Adverse Reactions (6.1)].

Embryo-Fetal Toxicity

Advise pregnant women of the potential risk to a fetus. Advise females of reproductive potential to inform their healthcare provider of a known or suspected pregnancy [see Warnings and Precautions (5.4), Use in Specific Populations (8.1)].

Advise females of reproductive potential to use effective contraception during treatment with ONUREG and for at least 6 months after the last dose [see Use in Specific Populations (8.3)].

Advise males with female partners of reproductive potential to use effective contraception during treatment with ONUREG and for at least 3 months after the last dose [see Use in Specific Populations (8.3)].

Lactation

Advise women not to breastfeed during treatment with ONUREG and for 1 week after the last dose [see Use in Specific Populations (8.2)].

Administration

Advise patients to take ONUREG with or without food at about the same time each day and how to make up a missed or vomited dose. Advise patients to swallow tablets whole. Advise patients not to cut, crush, or chew the tablets [see Dosage and Administration (2.2)].

Storage Instructions

Advise patients to keep ONUREG in the original container (bottles or blisters). If bottles are dispensed, advise patients to keep the container tightly closed with both desiccant canisters inside and to not eat the desiccant canisters [see How Supplied/Storage and Handling (16)].

Marketed by:
Bristol-Myers Squibb Company
Princeton, NJ 08543 USA

ONUREG® is a trademark of Celgene Corporation, a Bristol-Myers Squibb company.

ONUPI.004

Patient Information
ONUREG® (on-u-reg)
(azacitidine) tablets, for oral use

What is ONUREG?

ONUREG is a prescription medicine used for continued treatment of adults with acute myeloid leukemia (AML) who:

- had a first complete remission (CR) following intensive induction chemotherapy with or without recovery of your blood cell counts, and
- who are not able to complete intensive curative therapy.

It is not known if ONUREG is safe and effective in children under 18 years of age.

Do not take ONUREG if you:

- are allergic to azacitidine or any of the ingredients in ONUREG. See the end of this leaflet for a complete list of ingredients in ONUREG.

Before taking ONUREG, tell your healthcare provider about all of your medical conditions, including if you:

- have kidney or liver problems.
- are pregnant or plan to become pregnant. ONUREG can harm your unborn baby.
  Females who are able to become pregnant:
  - Your healthcare provider should perform a pregnancy test before you start treatment with ONUREG.
  - You should use effective birth control (contraception) during treatment and for at least 6 months after your last dose of ONUREG.
  - Tell your healthcare provider right away if you become pregnant during treatment with ONUREG.
Males with a female sexual partner who can become pregnant:
  1. You should use effective birth control (contraception) during treatment and for at least 3 months after your last dose of ONUREG.
- are breastfeeding or plan to breastfeed. It is not known if ONUREG passes into your breast milk. Do not breastfeed during treatment and for 1 week after your last dose of ONUREG.

Tell your healthcare provider about all the medicines you take, including prescription and over-the-counter medicines, vitamins, and herbal supplements.

How should I take ONUREG?

- Take ONUREG exactly as your healthcare provider tells you to take it.
- Your healthcare provider will prescribe an anti-nausea medicine for you to take to help prevent nausea and vomiting during your treatment with ONUREG.
  - Take the anti-nausea medicine 30 minutes before each dose of ONUREG.
  - Your healthcare provider may decide to stop the anti-nausea medicine after your second cycle of ONUREG, if you do not have any nausea or vomiting.
- Take ONUREG by mouth 1 time each day beginning on Day 1 through Day 14 of each 28-day cycle.
- Take ONUREG with or without food at about the same time each day.
- Swallow ONUREG tablets whole. Do not cut, crush, or chew the tablets.
- If the powder from ONUREG tablets comes in contact with your skin, wash the area well right away with soap and water.
- If the powder from ONUREG tablets comes in contact with your eyes or mouth (mucous membranes), flush the area right away with water.
- If you miss a dose of ONUREG, or if you do not take your dose at the usual time, take the dose as soon as possible that day. Take your next dose at the regular time the next day. Do not take 2 doses on the same day to make up for a missed dose.
- If you vomit after taking a dose of ONUREG, do not take another dose on the same day. Take your next dose at the regular time the next day.

What are the possible side effects of ONUREG?

ONUREG can cause serious side effects, including:

- New or worsening low white blood cell counts (neutropenia). New or worsening low white blood cell counts are common but can also be severe during treatment with ONUREG. If your white blood cell counts become very low, you are at increased risk for infections. Your healthcare provider will check your white blood cell counts before and during treatment with ONUREG. Your healthcare provider may prescribe a medicine to help increase your white blood cell count if needed.
  Tell your healthcare provider right away if you get any of the following symptoms:

- fever or chills
- body aches

- feeling very tired or weak
- unusual headaches

- New or worsening low platelet counts (thrombocytopenia). Low platelet counts are common but can also be severe during treatment with ONUREG. Your healthcare provider will check your platelet counts before and during treatment with ONUREG. Tell your healthcare provider right away if you have any unusual bruising or bleeding. Your healthcare provider may change your dose or tell you to stop taking ONUREG if you have low blood cell counts.

ONUREG may cause fertility problems in males and females, which may affect your ability to have children. Talk with your healthcare provider if you have concerns about fertility.

The most common side effects of ONUREG include:

- nausea and vomiting. See "How should I take ONUREG?"
- diarrhea. You may need to be treated with anti-diarrheal medicines.
- tiredness or weakness
- constipation
- stomach area (abdominal) pain

- pneumonia
- joint pain
- decreased appetite
- pain in arms or legs
- dizziness

These are not all of the possible side effects of ONUREG. Call your doctor for medical advice about side effects. You may report side effects to FDA at 1-800-FDA-1088.

How should I store ONUREG?

- Store bottles or blisters of ONUREG tablets at room temperature between 68°F to 77°F (20°C to 25°C).
- Store ONUREG tablets in the original bottle or the original aluminum-aluminum blisters.
- Bottles of ONUREG contain 2 drying agent (desiccant) canisters. Do not eat the desiccant canisters.
- Keep the ONUREG bottle tightly closed.
- Talk to your healthcare provider about how to safely throw away (dispose of) any unused or expired ONUREG.

Keep ONUREG and all medicines out of the reach of children

General information about the safe and effective use of ONUREG.

Medicines are sometimes prescribed for purposes other than those listed in a Patient Information leaflet. Do not use ONUREG for a condition for which it was not prescribed. Do not give ONUREG to other people, even if they have the same symptoms you have. It may harm them. You can ask your pharmacist or healthcare provider for information about ONUREG that is written for health professionals.

What are the ingredients in ONUREG?

Active ingredient: azacitidine

Inactive ingredients:

Each core tablet contains: croscarmellose sodium, magnesium stearate, mannitol, and silicified microcrystalline cellulose.

The pink 200 mg tablet coating contains: hypromellose, iron oxide red, lactose monohydrate, polyethylene glycol, titanium dioxide, and triacetin.

The brown 300 mg tablet coating contains: black iron oxide, hypromellose, iron oxide red, iron oxide yellow, lactose monohydrate, polyethylene glycol, titanium dioxide, and triacetin.

Marketed by: Bristol-Myers Squibb Company, Princeton, NJ 08543 USA
ONUREG® is a trademark of Celgene Corporation, a Bristol-Myers Squibb company.
ONUPPI V4 10/2022
For more information, go to www.ONUREG.com or call 1-800-721-5072.

This Patient Information has been approved by the U.S. Food and Drug Administration.
Revised: October 2022

PRINCIPAL DISPLAY PANEL - 200 mg Bottle Label

NDC 59572-730-14

ONUREG™
(azacitidine) tablets

200 mg

Swallow tablets whole.
Do not cut, crush, or chew the tablets.

Rx only
14 Tablets

CAUTION: Hazardous Agent

PRINCIPAL DISPLAY PANEL - 200 mg Blister Pack Carton

NDC 59572-730-07
Rx only

ONUREG™
(azacitidine) tablets

200 mg

Each tablet contains 200 mg of azacitidine.

Swallow tablets whole. Do not cut, crush, or chew the tablets.

One Blister Card
Containing 7 Tablets

Bristol Myers Squibb

CAUTION: Hazardous Agent

PRINCIPAL DISPLAY PANEL - 300 mg Blister Pack Carton

NDC 59572-740-07
Rx only

ONUREG™
(azacitidine) tablets

300 mg

Each tablet contains 200 mg of azacitidine.

Swallow tablets whole. Do not cut, crush, or chew the tablets.

One Blister Card
Containing 7 Tablets

Bristol Myers Squibb

CAUTION: Hazardous Agent